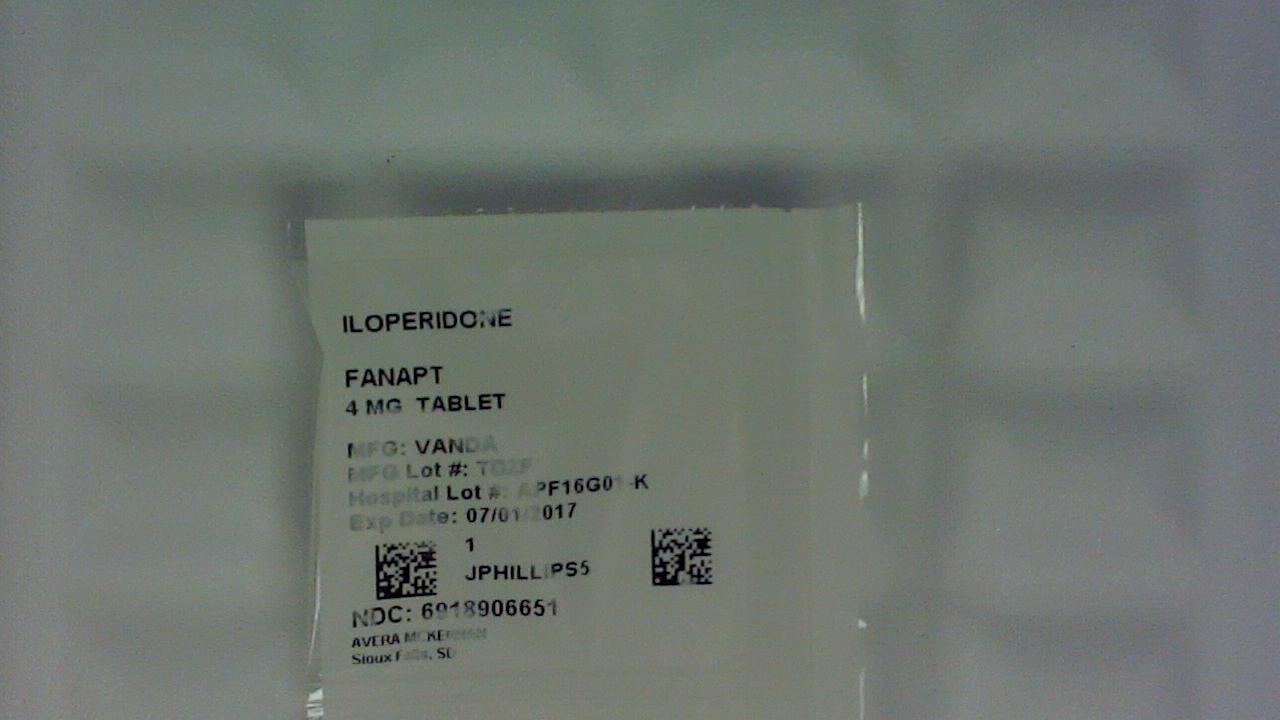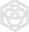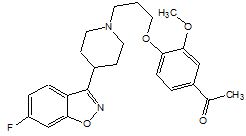 DRUG LABEL: Fanapt
NDC: 69189-0665 | Form: TABLET
Manufacturer: Avera McKennan Hospital
Category: prescription | Type: HUMAN PRESCRIPTION DRUG LABEL
Date: 20170328

ACTIVE INGREDIENTS: ILOPERIDONE 4 mg/1 1
INACTIVE INGREDIENTS: LACTOSE MONOHYDRATE; CELLULOSE, MICROCRYSTALLINE; HYPROMELLOSES; CROSPOVIDONE; SILICON DIOXIDE; MAGNESIUM STEARATE

HIGHLIGHTS OF PRESCRIBING INFORMATION

These highlights do not include all the information needed to use FANAPT safely and effectively. See full prescribing information for FANAPT.
FANAPT® (iloperidone) tablets
Initial U.S. Approval: 2009

RECENT MAJOR CHANGES

Contraindications (4) 1/2016

WARNING: INCREASED MORTALITY IN ELDERLY PATIENTS WITH DEMENTIA-RELATED PSYCHOSIS

See full prescribing information for complete boxed warning.

Elderly patients with dementia-related psychosis treated with antipsychotic drugs are at an increased risk of death. FANAPT is not approved for use in patients with dementia-related psychosis. (5.1)

1 INDICATIONS AND USAGE

FANAPT is an atypical antipsychotic agent indicated for the treatment of schizophrenia in adults. (1) Efficacy was established in two short-term (4- and 6-week) placebo- and active-controlled studies of adult patients with schizophrenia. (14) In choosing among treatments, prescribers should consider the ability of FANAPT to prolong the QT interval and the use of other drugs first. Prescribers should also consider the need to titrate FANAPT slowly to avoid orthostatic hypotension, which may lead to delayed effectiveness compared to some other drugs that do not require similar titration.

2 DOSAGE AND ADMINISTRATION

The recommended target dosage of FANAPT tablets is 12 to 24 mg/day administered twice daily. This target dosage range is achieved by daily dosage adjustments, alerting patients to symptoms of orthostatic hypotension, starting at a dose of 1 mg twice daily, then moving to 2 mg, 4 mg, 6 mg, 8 mg, 10 mg, and 12 mg twice daily on Days 2, 3, 4, 5, 6, and 7 respectively, to reach the 12 mg/day to 24 mg/day dose range. FANAPT can be administered without regard to meals. (2.1)

3 DOSAGE FORMS AND STRENGTHS

1 mg, 2 mg, 4 mg, 6 mg, 8 mg, 10 mg and 12 mg tablets. (3)

4 CONTRAINDICATIONS

Known hypersensitivity to FANAPT or to any components in the formulation. (4, 6.2)

5 WARNINGS AND PRECAUTIONS

- Elderly patients with dementia-related psychosis who are treated with atypical antipsychotic drugs are at an increased risk of death and cerebrovascular-related adverse events, including stroke. (5.1)
- QT prolongation: Prolongs QT interval and may be associated with arrhythmia and sudden death-consider using other antipsychotics first. Avoid use of FANAPT in combination with other drugs that are known to prolong QTc; use caution and consider dose modification when prescribing FANAPT with other drugs that inhibit FANAPT metabolism. Monitor serum potassium and magnesium in patients at risk for electrolyte disturbances. (1, 5.2, 7.1, 7.3, 12.3)
- Neuroleptic Malignant Syndrome: Manage with immediate discontinuation of drug and close monitoring. (5.3)
- Tardive dyskinesia: Discontinue if clinically appropriate. (5.4)
- Metabolic Changes: Atypical antipsychotic drugs have been associated with metabolic changes that may increase cardiovascular/cerebrovascular risk. These metabolic changes include hyperglycemia, dyslipidemia, and weight gain. (5.5)
  - Hyperglycemia and diabetes mellitus: Monitor patients for symptoms of hyperglycemia including polydipsia, polyuria, polyphagia, and weakness. Monitor glucose regularly in patients at risk for diabetes. (5.5)
  - Dyslipidemia: Undesirable alterations have been observed in patients treated with atypical antipsychotics. (5.5)
  - Weight Gain: Weight gain has been reported. Monitor weight. (5.5)
- Seizures: Use cautiously in patients with a history of seizures or with conditions that lower seizure threshold. (5.6)
- Orthostatic hypotension: Dizziness, tachycardia, and syncope can occur with standing. (5.7)
- Leukopenia, Neutropenia, and Agranulocytosis have been reported with antipsychotics. Patients with a pre-existing low white blood cell count (WBC) or a history of leukopenia/neutropenia should have their complete blood count (CBC) monitored frequently during the first few months of therapy and should discontinue FANAPT at the first sign of a decline in WBC in the absence of other causative factors. (5.8)
- Suicide: Close supervision of high risk patients. (5.12)
- Priapism: Cases have been reported in association with FANAPT treatment. (5.13)
- Potential for cognitive and motor impairment: Use caution when operating machinery. (5.14)
- See Full Prescribing Information for additional WARNINGS and PRECAUTIONS.

6 ADVERSE REACTIONS

Commonly observed adverse reactions (incidence ≥5% and 2-fold greater than placebo) were: dizziness, dry mouth, fatigue, nasal congestion, orthostatic hypotension, somnolence, tachycardia, and weight increased. (6.1)

To report SUSPECTED ADVERSE REACTIONS, contact Vanda Pharmaceuticals Inc. at 1-844-GO-VANDA (1-844-468-2632) or FDA at 1-800-FDA-1088 or www.fda.gov/medwatch.

7 DRUG INTERACTIONS

- The dose of FANAPT should be reduced in patients co-administered a strong CYP2D6 or CYP3A4 inhibitor. (2.2, 7.1)

8 USE IN SPECIFIC POPULATIONS

- Pregnancy: No human or animal data. Use only if clearly needed. (8.1)
- Nursing Mothers: Should not breastfeed. (8.3)
- Pediatric Use: Safety and effectiveness not established in children and adolescents. (8.4)
- Hepatic Impairment:. FANAPT is not recommended for patients with severe hepatic impairment. (2.2, 8.7)
- The dose of FANAPT should be reduced in patients who are poor metabolizers of CYP2D6. (2.2, 12.3)

FULL PRESCRIBING INFORMATION

WARNING: INCREASED MORTALITY IN ELDERLY PATIENTS WITH DEMENTIA-RELATED PSYCHOSIS

Elderly patients with dementia-related psychosis treated with antipsychotic drugs are at an increased risk of death. Analysis of seventeen placebo-controlled trials (modal duration 10 weeks), largely in patients taking atypical antipsychotic drugs, revealed a risk of death in the drug-treated patients of between 1.6 to 1.7 times the risk of death in placebo-treated patients. Over the course of a typical 10-week controlled trial, the rate of death in drug-treated patients was about 4.5%, compared to a rate of about 2.6% in the placebo group. Although the causes of death were varied, most of the deaths appeared to be either cardiovascular (e.g., heart failure, sudden death) or infectious (e.g., pneumonia) in nature.

Observational studies suggest that, similar to atypical antipsychotic drugs, treatment with conventional antipsychotic drugs may increase mortality. The extent to which the findings of increased mortality in observational studies may be attributed to the antipsychotic drug as opposed to some characteristic(s) of the patients is not clear. FANAPT is not approved for the treatment of patients with Dementia-Related Psychosis [see Warnings and Precautions (5.1)].

1 INDICATIONS AND USAGE

FANAPT® tablets are indicated for the treatment of adults with schizophrenia. Efficacy was established in two short-term (4- and 6-week) placebo-and active-controlled studies of adult patients with schizophrenia [see Clinical Studies (14)].

When deciding among the alternative treatments available for this condition, the prescriber should consider the finding that FANAPTis associated with prolongation of the QTc interval [see Warnings and Precautions (5.2)]. Prolongation of the QTc interval is associated in some other drugs with the ability to cause torsade de pointes-type arrhythmia, a potentially fatal polymorphic ventricular tachycardia which can result in sudden death. In many cases this would lead to the conclusion that other drugs should be tried first. Whether FANAPT will cause torsade de pointes or increase the rate of sudden death is not yet known.

Patients must be titrated to an effective dose of FANAPT.Thus, control of symptoms may be delayed during the first 1 to 2 weeks of treatment compared to some other antipsychotic drugs that do not require a similar titration. Prescribers should be mindful of this delay when selecting an antipsychotic drug for the treatment of schizophrenia [see Dosage and Administration (2.1) and Clinical Studies (14)].

The effectiveness of FANAPT in long-term use, that is, for more than 6 weeks, has not been systematically evaluated in controlled trials. Therefore, the physician who elects to use FANAPT for extended periods should periodically re-evaluate the long-term usefulness of the drug for the individual patient [see Dosage and Administration (2.3)].

2 DOSAGE AND ADMINISTRATION

2.1 Usual Dose

FANAPT must be titrated slowly from a low starting dose to avoid orthostatic hypotension due to its alpha-adrenergic blocking properties. The recommended starting dose for FANAPT tablets is 1 mg twice daily. Dose increases to reach the target range of 6-12 mg twice daily (12_24 mg/day) may be made with daily dosage adjustments not to exceed 2 mg twice daily (4 mg/day). The maximum recommended dose is 12 mg twice daily (24 mg/day). FANAPT doses above 24 mg/day have not been systematically evaluated in the clinical trials. Efficacy was demonstrated with FANAPT in a dose range of 6 to 12 mg twice daily. Prescribers should be mindful of the fact that patients need to be titrated to an effective dose of FANAPT. Thus, control of symptoms may be delayed during the first 1 to 2 weeks of treatment compared to some other antipsychotic drugs that do not require similar titration. Prescribers should also be aware that some adverse effects associated with FANAPT use are dose related.

FANAPT can be administered without regard to meals.

2.2 Dosage in Special Populations

Dosage adjustments are not routinely indicated on the basis of age, gender, race, or renal impairment status [see Use in Specific Populations (8.6, 8.7)].

Dosage adjustment for patients taking FANAPT concomitantly with potential CYP2D6 inhibitors: FANAPT dose should be reduced by one-half when administered concomitantly with strong CYP2D6 inhibitors such as fluoxetine or paroxetine. When the CYP2D6 inhibitor is withdrawn from the combination therapy, FANAPT dose should then be increased to where it was before [see Drug Interactions (7.1)].

Dosage adjustment for patients taking FANAPT concomitantly with potential CYP3A4 inhibitors: FANAPT dose should be reduced by one-half when administered concomitantly with strong CYP3A4 inhibitors such as ketoconazole or clarithromycin. When the CYP3A4 inhibitor is withdrawn from the combination therapy, FANAPT dose should be increased to where it was before [see Drug Interactions (7.1)].

Dosage adjustment for patients taking FANAPT who are poor metabolizers of CYP2D6: FANAPT dose should be reduced by one-half for poor metabolizers of CYP2D6 [see Clinical Pharmacology, Pharmacokinetics (12.3)].

Hepatic Impairment: No dose adjustment to FANAPT is needed in patients with mild hepatic impairment. Exercise caution when administering it to patients with moderate hepatic impairment. FANAPT is not recommended for patients with severe hepatic impairment [see Use in Specific Populations (8.7)].

2.3 Maintenance Treatment

Although there is no body of evidence available to answer the question of how long the patient treated with FANAPT should be maintained, it is generally recommended that responding patients be continued beyond the acute response. Patients should be periodically reassessed to determine the need for maintenance treatment.

2.4 Reinitiation of Treatment in Patients Previously Discontinued

Although there are no data to specifically address reinitiation of treatment, it is recommended that the initiation titration schedule be followed whenever patients have had an interval off FANAPT of more than 3 days.

2.5 Switching from Other Antipsychotics

There are no specific data to address how patients with schizophrenia can be switched from other antipsychotics to FANAPT or how FANAPT can be used concomitantly with other antipsychotics. Although immediate discontinuation of the previous antipsychotic treatment may be acceptable for some patients with schizophrenia, more gradual discontinuation may be most appropriate for others. In all cases, the period of overlapping antipsychotic administration should be minimized.

3 DOSAGE FORMS AND STRENGTHS

FANAPT tablets are available in the following strengths: 1 mg, 2 mg, 4 mg, 6 mg, 8 mg, 10 mg, and 12 mg. The tablets are white, round, flat, beveled-edged and identified with a logo “” debossed on one side and tablet strength “1”, “2”, “4”, “6”, “8”, “10”, or “12” debossed on the other side.

4 CONTRAINDICATIONS

FANAPT is contraindicated in individuals with a known hypersensitivity reaction to the product. Anaphylaxis, angioedema, and other hypersensitivity reactions have been reported [see Adverse Reactions (6.2)].

5 WARNINGS AND PRECAUTIONS

5.1 Increased Risks in Elderly Patients with Dementia-Related Psychosis

Increased Mortality

Elderly patients with dementia-related psychosis treated with atypical antipsychotic drugs are at an increased risk of death compared to placebo. FANAPT is not approved for the treatment of patients with dementia-related psychosis [see Boxed Warning].

Cerebrovascular Adverse Events, Including Stroke

In placebo-controlled trials with risperidone, aripiprazole, and olanzapine in elderly patients with dementia, there was a higher incidence of cerebrovascular adverse events (cerebrovascular accidents and transient ischemic attacks) including fatalities compared to placebo-treated patients. FANAPT is not approved for the treatment of patients with dementia-related psychosis [see Boxed Warning].

5.2 QT Prolongation

In an open-label QTc study in patients with schizophrenia or schizoaffective disorder (n=160), FANAPT was associated with QTc prolongation of 9 msec at an iloperidone dose of 12 mg twice daily. The effect of FANAPT on the QT interval was augmented by the presence of CYP450 2D6 or 3A4 metabolic inhibition (paroxetine 20 mg once daily and ketoconazole 200 mg twice daily, respectively). Under conditions of metabolic inhibition for both 2D6 and 3A4, FANAPT 12 mg twice daily was associated with a mean QTcF increase from baseline of about 19 msec.

No cases of torsade de pointes or other severe cardiac arrhythmias were observed during the pre-marketing clinical program.

The use of FANAPT should be avoided in combination with other drugs that are known to prolong QTc including Class 1A (e.g., quinidine, procainamide) or Class III (e.g., amiodarone, sotalol) antiarrhythmic medications, antipsychotic medications (e.g., chlorpromazine, thioridazine), antibiotics (e.g., gatifloxacin, moxifloxacin), or any other class of medications known to prolong the QTc interval (e.g., pentamidine, levomethadyl acetate, methadone). FANAPT should also be avoided in patients with congenital long QT syndrome and in patients with a history of cardiac arrhythmias.

Certain circumstances may increase the risk of torsade de pointes and/or sudden death in association with the use of drugs that prolong the QTc interval, including (1) bradycardia; (2) hypokalemia or hypomagnesemia; (3) concomitant use of other drugs that prolong the QTc interval; and (4) presence of congenital prolongation of the QT interval; (5) recent acute myocardial infarction; and/or (6) uncompensated heart failure.

Caution is warranted when prescribing FANAPT with drugs that inhibit FANAPT metabolism [see Drug Interactions (7.1)], and in patients with reduced activity of CYP2D6 [see Clinical Pharmacology (12.3)].

It is recommended that patients being considered for FANAPT treatment who are at risk for significant electrolyte disturbances have baseline serum potassium and magnesium measurements with periodic monitoring. Hypokalemia (and/or hypomagnesemia) may increase the risk of QT prolongation and arrhythmia. FANAPT should be avoided in patients with histories of significant cardiovascular illness, e.g., QT prolongation, recent acute myocardial infarction, uncompensated heart failure, or cardiacarrhythmia. FANAPT should be discontinued in patients who are found to have persistent QTc measurements >500 msec.

If patients taking FANAPT experience symptoms that could indicate the occurrence of cardiac arrhythmias, e.g., dizziness, palpitations, or syncope, the prescriber should initiate further evaluation, including cardiac monitoring.

5.3 Neuroleptic Malignant Syndrome (NMS)

A potentially fatal symptom complex sometimes referred to as Neuroleptic Malignant Syndrome (NMS) has been reported in association with administration of antipsychotic drugs, including FANAPT. Clinical manifestations include hyperpyrexia, muscle rigidity, altered mental status (including catatonic signs) and evidence of autonomic instability (irregular pulse or blood pressure, tachycardia, diaphoresis, and cardiac dysrhythmia). Additional signs may include elevated creatine phosphokinase, myoglobinuria (rhabdomyolysis), and acute renal failure.

The diagnostic evaluation of patients with this syndrome is complicated. In arriving at a diagnosis, it is important to identify cases in which the clinical presentation includes both serious medical illness (e.g., pneumonia, systemic infection, etc.) and untreated or inadequately treated extrapyramidal signs and symptoms (EPS). Other important considerations in the differential diagnosis include central anticholinergic toxicity, heat stroke, drug fever, and primary central nervous system (CNS) pathology.

The management of this syndrome should include: (1) immediate discontinuation of the antipsychotic drugs and other drugs not essential to concurrent therapy, (2) intensive symptomatic treatment and medical monitoring, and (3) treatment of any concomitant serious medical problems for which specific treatments are available. There is no general agreement about specific pharmacological treatment regimens for NMS.

If a patient requires antipsychotic drug treatment after recovery from NMS, the potential reintroduction of drug therapy should be carefully considered. The patient should be carefully monitored, since recurrences of NMS have been reported.

5.4 Tardive Dyskinesia

Tardive dyskinesia is a syndrome consisting of potentially irreversible, involuntary, dyskinetic movements, which may develop in patients treated with antipsychotic drugs. Although the prevalence of the syndrome appears to be highest among the elderly, especially elderly women, it is impossible to rely on prevalence estimates to predict, at the inception of antipsychotic treatment, which patients are likely to develop the syndrome. Whether antipsychotic drug products differ in their potential to cause tardive dyskinesia is unknown.

The risk of developing tardive dyskinesia and the likelihood that it will become irreversible are believed to increase as the duration of treatment and the total cumulative dose of antipsychotic administered increases. However, the syndrome can develop, although much less commonly, after relatively brief treatment periods at low doses.

There is no known treatment for established cases of tardive dyskinesia, although the syndrome may remit, partially or completely, if antipsychotic treatment is withdrawn. Antipsychotic treatment itself, however, may suppress (or partially suppress) the signs and symptoms of the syndrome and thereby may possibly mask the underlying process. The effect that symptomatic suppression has upon the long-term course of the syndrome is unknown.

Given these considerations, FANAPT should be prescribed in a manner that is most likely to minimize the occurrence of tardive dyskinesia. Chronic antipsychotic treatment should generally be reserved for patients who suffer from a chronic illness that (1) is known to respond to antipsychotic drugs, and (2) for whom alternative, equally effective, but potentially less harmful treatments are not available or appropriate. In patients who do require chronic treatment, the smallest dose and the shortest duration of treatment producing a satisfactory clinical response should be sought. The need for continued treatment should be reassessed periodically.

If signs and symptoms of tardive dyskinesia appear in a patient on FANAPT, drug discontinuation should be considered. However, some patients may require treatment with FANAPT despite the presence of the syndrome.

5.5 Metabolic Changes

Atypical antipsychotic drugs have been associated with metabolic changes that may increase cardiovascular/cerebrovascular risk. These metabolic changes include hyperglycemia, dyslipidemia, and body weight gain [see Patient Counseling Information (17.3)]. While all atypical antipsychotic drugs have been shown to produce some metabolic changes, each drug in the class has its own specific risk profile.

Hyperglycemia and Diabetes Mellitus

Hyperglycemia, in some cases extreme and associated with ketoacidosis or hyperosmolar coma or death, has been reported in patients treated with atypical antipsychotics including FANAPT. Assessment of the relationship between atypical antipsychotic use and glucose abnormalities is complicated by the possibility of an increased background risk of diabetes mellitus in patients with schizophrenia and the increasing incidence of diabetes mellitus in the general population. Given these confounders, the relationship between atypical antipsychotic use and hyperglycemia-related adverse events is not completely understood. However, epidemiological studies suggest an increased risk of treatment-emergent hyperglycemia-related adverse events in patients treated with the atypical antipsychotics included in these studies. Because FANAPT was not marketed at the time these studies were performed, it is not known if FANAPT is associated with this increased risk.

Patients with an established diagnosis of diabetes mellitus who are started on atypical antipsychotics should be monitored regularly for worsening of glucose control. Patients with risk factors for diabetes mellitus (e.g., obesity, family history of diabetes) who are starting treatment with atypical antipsychotics should undergo fasting blood glucose testing at the beginning of treatment and periodically during treatment. Any patient treated with atypical antipsychotics should be monitored for symptoms of hyperglycemia including polydipsia, polyuria, polyphagia, and weakness. Patients who develop symptoms of hyperglycemia during treatment with atypical antipsychotics should undergo fasting blood glucose testing. In some cases, hyperglycemia has resolved when the atypical antipsychotic was discontinued; however, some patients required continuation of antidiabetic treatment despite discontinuation of the suspect drug.

Data from a 4-week, fixed-dose study in adult subjects with schizophrenia, in which fasting blood samples were drawn,are presented in Table 1.

Table 1: Change in Fasting Glucose
 |  | FANAPT
 | Placebo | 24 mg/day
 | Mean Change from Baseline(mg/dL)
 | n=114 | n=228
Serum Glucose Change from Baseline | -0.5 | 6.6
 | Proportion of Patients with Shifts
Serum Glucose Normal to High | 2.5 % | 10.7 %
(<100 mg/dL to ≥126 mg/dL) | (2/80) | (18/169)

Pooled analyses of glucose data from clinical studies including longer term trials are shown in Table 2.

Table 2: Change in Glucose
Mean Change from Baseline (mg/dL)
 | 3-6 months | 6-12 months | >12 months
FANAPT 10-16 mg/day | 1.8 (N=773) | 5.4 (N=723) | 5.4 (N=425)
FANAPT 20-24 mg/day | -3.6 (N=34) | -9.0 (N=31) | -18.0 (N=20)

Dyslipidemia

Undesirable alterations in lipids have been observed in patients treated with atypical antipsychotics.

Data from a placebo-controlled, 4-week, fixed-dose study, in which fasting blood samples were drawn, in adult subjects with schizophrenia are presented in Table 3.

Table 3: Change in Fasting Lipids
 |  | FANAPT
 | Placebo | 24 mg/day
 | Mean Change from Baseline (mg/dL)
Cholesterol | n= 114 | n=228
Change from baseline | -2.17 | 8.18
LDL | n=109 | n=217
Change from baseline | -1.41 | 9.03
HDL | n= 114 | n=228
Change from baseline | -3.35 | 0.55
Triglycerides | n= 114 | n=228
Change from baseline | 16.47 | -0.83
 | Proportion of Patients with Shifts
Cholesterol
Normal to High | 1.4% | 3.6%
(<200 mg/dL to ≥240 mg/dL) | (1/72) | (5/141)
LDL
Normal to High | 2.4% | 1.1%
(<100 mg/dL to ≥160 mg/dL) | (1/42) | (1/90)
HDL
Normal to Low | 23.8% | 12.1%
(≥40 mg/dL to <40 mg/dL) | (19/80) | (20/166)
Triglycerides
Normal to High | 8.3% | 10.1%
(<150 mg/dL to ≥200 mg/dL) | (6/72) | (15/148)

Pooled analyses of cholesterol and triglyceride data from clinical studies including longer term trials are shown in Tables 4 and 5.

Table 4: Change in Cholesterol
Mean Change from Baseline (mg/dL)
 | 3-6 months | 6-12 months | >12 months
FANAPT 10-16 mg/day | -3.9 (N=783) | -3.9 (N=726) | -7.7 (N=428)
FANAPT 20-24 mg/day | -19.4 (N=34) | -23.2 (N=31) | -19.4 (N=20)

Table 5: Change in Triglycerides
Mean Change from Baseline (mg/dL)
 | 3-6 months | 6-12 months | >12 months
FANAPT 10-16 mg/day | -8.9 (N=783) | -8.9 (N=726) | -17.7 (N=428)
FANAPT 20-24 mg/day | -26.6 (N=34) | -35.4 (N=31) | -17.7 (N=20)

Weight Gain

Weight gain has been observed with atypical antipsychotic use. Clinical monitoring of weight is recommended.

Across all short- and long-term studies, the overall mean change from baseline at endpoint was 2.1 kg.

Changes in body weight (kg) and the proportion of subjects with ≥7% gain in body weight from 4 placebo-controlled, 4- or 6-week, fixed- or flexible-dose studies in adult subjects are presented in Table 6.

Table 6: Change in Body Weight
 |  | FANAPT | FANAPT
 | Placebo | 10-16 mg/day | 20-24 mg/day
 | n=576 | n=481 | n=391
Weight (kg)
Change from Baseline | -0.1 | 2.0 | 2.7
Weight Gain
≥7% increase from Baseline | 4% | 12% | 18%

5.6 Seizures

In short-term placebo-controlled trials (4- to 6-weeks), seizures occurred in 0.1% (1/1344) of patients treated with FANAPT compared to 0.3% (2/587) on placebo. As with other antipsychotics, FANAPT should be used cautiously in patients with a history of seizures or with conditions that potentially lower the seizure threshold, e.g., Alzheimer’s dementia. Conditions that lower the seizure threshold may be more prevalent in a population of 65 years or older.

5.7 Orthostatic Hypotension and Syncope

FANAPT can induce orthostatic hypotension associated with dizziness, tachycardia, and syncope. This reflects its alpha1-adrenergic antagonist properties. In double-blind placebo-controlled short-term studies, where the dose was increased slowly, as recommended above, syncope was reported in 0.4% (5/1344) of patients treated with FANAPT, compared with 0.2% (1/587) on placebo. Orthostatic hypotension was reported in 5% of patients given 20-24 mg/day, 3% of patients given 10-16 mg/day, and 1% of patients given placebo. More rapid titration would be expected to increase the rate of orthostatic hypotension and syncope.

FANAPT should be used with caution in patients with known cardiovascular disease (e.g., heart failure, history of myocardial infarction, ischemia, or conduction abnormalities), cerebrovascular disease, or conditions that predispose the patient to hypotension (dehydration, hypovolemia, and treatment with antihypertensive medications). Monitoring of orthostatic vital signs should be considered in patients who are vulnerable to hypotension.

5.8 Leukopenia, Neutropenia and Agranulocytosis

In clinical trial and postmarketing experience, events of leukopenia/neutropenia have been reported temporally related to antipsychotic agents. Agranulocytosis (including fatal cases) has also been reported.

Possible risk factors for leukopenia/neutropenia include preexisting low white blood cell count (WBC) and history of drug induced leukopenia/neutropenia. Patients with a pre-existing low WBC or a history of drug induced leukopenia/neutropenia should have their complete blood count (CBC) monitored frequently during the first few months of therapy and should discontinue FANAPT at the first sign of a decline in WBC in the absence of other causative factors.

Patients with neutropenia should be carefully monitored for fever or other symptoms or signs of infection and treated promptly if such symptoms or signs occur. Patients with severe neutropenia (absolute neutrophil count <1000/mm^3) should discontinue FANAPT and have their WBC followed until recovery.

5.9 Hyperprolactinemia

As with other drugs that antagonize dopamine D2 receptors, FANAPT elevates prolactin levels.

Hyperprolactinemia may suppress hypothalamicGnRH, resulting in reduced pituitary gonadotropin secretion. This, in turn, may inhibit reproductive function by impairing gonadalsteroidogenesis in both female and male patients. Galactorrhea, amenorrhea, gynecomastia, and impotence have been reported with prolactin-elevating compounds. Long-standing hyperprolactinemia when associated with hypogonadism may lead to decreased bone density in both female and male patients.

Tissue culture experiments indicate that approximately one-third of human breast cancers are prolactin-dependent in vitro, a factor of potential importance if the prescription of these drugs is contemplated in a patient with previously detected breast cancer. Mammary gland proliferative changes and increases in serum prolactin were seen in mice and rats treated with FANAPT [see Nonclinical Toxicology (13.1)]. Neither clinical studies nor epidemiologic studies conducted to date have shown an association between chronic administration of this class of drugs and tumorigenesis in humans; the available evidence is considered too limited to be conclusive at this time.

In a short-term placebo-controlled trial (4-weeks), the mean change from baseline to endpoint in plasma prolactin levels for the FANAPT 24 mg/day-treated group was an increase of 2.6 ng/mL compared to a decrease of 6.3 ng/mL in the placebo-group. In this trial, elevated plasma prolactin levels were observed in 26% of adults treated with FANAPT compared to 12% in the placebo group. In the short-term trials, FANAPT was associated with modest levels of prolactin elevation compared to greater prolactin elevations observed with some other antipsychotic agents. In pooled analysis from clinical studies including longer term trials, in 3210 adults treated with iloperidone, gynecomastia was reported in 2 male subjects (0.1%) compared to 0% in placebo-treated patients, and galactorrhea was reported in 8 female subjects (0.2%) compared to 3 female subjects (0.5%) in placebo-treated patients.

5.10 Body Temperature Regulation

Disruption of the body’s ability to reduce core body temperature has been attributed to antipsychotic agents. Appropriate care is advised when prescribing FANAPT for patients who will be experiencing conditions which may contribute to an elevation in core body temperature, e.g., exercising strenuously, exposure to extreme heat, receiving concomitant medication with anticholinergic activity, or being subject to dehydration.

5.11 Dysphagia

Esophageal dysmotility and aspiration have been associated with antipsychotic drug use. Aspiration pneumonia is a common cause of morbidity and mortality in elderly patients, in particular those with advanced Alzheimer’s dementia. FANAPT and other antipsychotic drugs should be used cautiously in patients at risk for aspiration pneumonia [see Boxed Warning].

5.12 Suicide

The possibility of a suicide attempt is inherent in psychotic illness, and close supervision of high-risk patients should accompany drug therapy. Prescriptions for FANAPT should be written for the smallest quantity of tablets consistent with good patient management in order to reduce the risk of overdose.

5.13 Priapism

Three cases of priapism were reported in the pre-marketing FANAPT program. Drugs with alpha-adrenergic blocking effects have been reported to induce priapism. FANAPT shares this pharmacologic activity. Severe priapism may require surgical intervention.

5.14 Potential for Cognitive and Motor Impairment

FANAPT, like other antipsychotics, has the potential to impair judgment, thinking or motor skills. In short-term, placebo-controlled trials, somnolence (including sedation) was reported in 11.9% (104/874) of adult patients treated with FANAPTat doses of 10 mg/day or greater versus 5.3% (31/587) treated with placebo. Patients should be cautioned about operating hazardous machinery, including automobiles, until they are reasonably certain that therapy with FANAPT does not affect them adversely.

6 ADVERSE REACTIONS

6.1 Clinical Studies Experience

Because clinical trials are conducted under widely varying conditions, adverse reaction rates observed in the clinical trial of a drug cannot be directly compared to rates in the clinical trials of another drug and may not reflect the rates observed in clinical practice. The information below is derived from a clinical trial database for FANAPT consisting of 2070 patients exposed to FANAPT at doses of 10 mg/day or greater, for the treatment of schizophrenia. Of these, 806 received FANAPT for at least 6 months, with 463 exposed to FANAPT for at least 12 months. All of these patients who received FANAPT were participating in multiple-dose clinical trials. The conditions and duration of treatment with FANAPT varied greatly and included (in overlapping categories), open-label and double-blind phases of studies, inpatients and outpatients, fixed-dose and flexible-dose studies, and short-term and longer-term exposure.

Adverse reactions during exposure were obtained by general inquiry and recorded by clinical investigators using their own terminology. Consequently, to provide a meaningful estimate of the proportion of individuals experiencing adverse reactions, reactions were grouped in standardized categories using MedDRA terminology.

The stated frequencies of adverse reactions represent the proportions of individuals who experienced a treatment-emergent adverse reaction of the type listed. A reaction was considered treatment emergent if it occurred for the first time or worsened while receiving therapy following baseline evaluation.

The information presented in these sections was derived from pooled data from 4 placebo-controlled, 4- or 6-week, fixed- or flexible-dose studies in patients who received FANAPT at daily doses within a range of 10 to 24 mg (n=874).

Adverse Reactions Occurring at an Incidence of 2% or More among FANAPT-Treated Patientsand More Frequent than Placebo

Table 7 enumerates the pooled incidences of treatment-emergent adverse reactions that were spontaneously reported in four placebo-controlled, 4- or 6-week, fixed- or flexible-dose studies, listing those reactions that occurred in 2% or more of patients treated with FANAPT in any of the dose groups, and for which the incidence in FANAPT-treated patients in any dose group was greater than the incidence in patients treated with placebo.

Table 7: Percentage of Treatment-Emergent Adverse Reactions in Short-Term, Fixed- or Flexible-Dose, Placebo-Controlled Trials in Adult Patients*
Body System or Organ Class | Placebo (%) | FANAPT 10-16 mg/day (%) | FANAPT 20-24 mg/day (%)
Dictionary-derived Term | (N=587) | (N=483) | (N=391)
Body as a Whole
Arthralgia | 2 | 3 | 3
Fatigue | 3 | 4 | 6
Musculoskeletal Stiffness | 1 | 1 | 3
Weight Increased | 1 | 1 | 9
Cardiac Disorders
Tachycardia | 1 | 3 | 12
Eye Disorders
Vision Blurred | 2 | 3 | 1
Gastrointestinal Disorders
Nausea | 8 | 7 | 10
Dry Mouth | 1 | 8 | 10
Diarrhea | 4 | 5 | 7
Abdominal Discomfort | 1 | 1 | 3
Infections
Nasopharyngitis | 3 | 4 | 3
Upper Respiratory Tract Infection | 1 | 2 | 3
Nervous System Disorders
Dizziness | 7 | 10 | 20
Somnolence | 5 | 9 | 15
Extrapyramidal Disorder | 4 | 5 | 4
Tremor | 2 | 3 | 3
Lethargy | 1 | 3 | 1
Reproductive System
Ejaculation Failure | <1 | 2 | 2
Respiratory
Nasal Congestion | 2 | 5 | 8
Dyspnea | <1 | 2 | 2
Skin
Rash | 2 | 3 | 2
Vascular Disorders
Orthostatic Hypotension | 1 | 3 | 5
Hypotension | <1 | <1 | 3

* Table includes adverse reactions that were reported in 2% or more of patients in any of the FANAPT dose groups and which occurred at greater incidence than in the placebo group. Figures rounded to the nearest integer.

Dose-Related Adverse Reactions in Clinical Trials

Based on the pooled data from 4 placebo-controlled, 4- or 6-week, fixed- or flexible-dose studies, adverse reactions that occurred with a greater than 2% incidence in the patients treated with FANAPT, and for which the incidence in patients treated with FANAPT20-24 mg/day were twice than the incidence in patients treated with FANAPT 10-16 mg/day were: abdominal discomfort, dizziness, hypotension, musculoskeletal stiffness, tachycardia, and weight increased.

Common and Drug-Related Adverse Reactions in Clinical Trials

Based on the pooled data from 4 placebo-controlled, 4- or 6-week, fixed- or flexible-dose studies, the following adverse reactions occurred in ≥5% incidence in the patients treated with FANAPT and at least twice the placebo rate for at least 1 dose: dizziness, dry mouth, fatigue, nasal congestion, somnolence, tachycardia, orthostatic hypotension, and weight increased. Dizziness, tachycardia, and weight increased were at least twice as common on 20-24 mg/day as on 10-16 mg/day.

Extrapyramidal Symptoms (EPS) in Clinical Trials

Pooled data from the 4 placebo-controlled, 4- or 6-week, fixed- or flexible-dose studies provided information regarding treatment-emergent EPS. Adverse event data collected from those trials showed the following rates of EPS-related adverse events as shown in Table 8.

Table 8: Percentage of EPS Compared to Placebo
 | Placebo (%) | FANAPT 10-16 mg/day (%) | FANAPT 20-24 mg/day (%)
Adverse Event Term | (N=587) | (N=483) | (N=391)
All EPS events | 11.6 | 13.5 | 15.1
Akathisia | 2.7 | 1.7 | 2.3
Bradykinesia | 0 | 0.6 | 0.5
Dyskinesia | 1.5 | 1.7 | 1.0
Dystonia | 0.7 | 1.0 | 0.8
Parkinsonism | 0 | 0.2 | 0.3
Tremor | 1.9 | 2.5 | 3.1

Adverse Reactions Associated with Discontinuation of Treatment in Clinical Trials

Based on the pooled data from 4 placebo-controlled, 4- or 6-week, fixed- or flexible-dose studies, there was no difference in the incidence of discontinuation due to adverse events between FANAPT-treated (5%) and placebo-treated (5%) patients. The types of adverse events that led to discontinuation were similar for the FANAPT- and placebo-treated patients.

Demographic Differences in Adverse Reactions in Clinical Trials

An examination of population subgroups in the 4 placebo-controlled, 4- or 6-week, fixed- or flexible-dose studies did not reveal any evidence of differences in safety on the basis of age, gender or race [see Warnings and Precautions (5.1)].

Laboratory Test Abnormalities in Clinical Trials

There were no differences between FANAPT and placebo in the incidence of discontinuation due to changes in hematology, urinalysis, or serum chemistry.

In short-term placebo-controlled trials (4- to 6-weeks), there were 1.0% (13/1342) iloperidone-treated patients with hematocrit at least one time below the extended normal range during post-randomization treatment, compared to 0.3% (2/585) on placebo. The extended normal range for lowered hematocrit was defined in each of these trials as the value 15% below the normal range for the centralized laboratory that was used in the trial.

Other Reactions During the Pre-marketing Evaluation of FANAPT

The following is a list of MedDRA terms that reflect treatment-emergent adverse reactions in patients treated with FANAPT at multiple doses ≥ 4 mg/day during any phase of a trial with the database of 3210 FANAPT-treated patients. All reported reactions are included except those already listed in Table 7, or other parts of the Adverse Reactions (6) section, those considered in the Warnings and Precautions (5), those reaction terms which were so general as to be uninformative, reactions reported in fewer than 3 patients and which were neither serious nor life-threatening, reactions that are otherwise common as background reactions, and reactions considered unlikely to be drug related. It is important to emphasize that, although the reactions reported occurred during treatment with FANAPT, they were not necessarily caused by it.

Reactions are further categorized by MedDRA system organ class and listed in order of decreasing frequency according to the following definitions: frequent adverse events are those occurring in at least 1/100 patients (only those not listed in Table 7 appear in this listing); infrequent adverse reactions are those occurring in 1/100 to 1/1000 patients; rare events are those occurring in fewer than 1/1000 patients.

Blood and Lymphatic Disorders: Infrequent – anemia, iron deficiency anemia; Rare – leukopenia

Cardiac Disorders: Frequent – palpitations; Rare – arrhythmia, atrioventricular block first degree, cardiac failure (including congestive and acute)

Ear and Labyrinth Disorders: Infrequent – vertigo, tinnitus

Endocrine Disorders: Infrequent – hypothyroidism

Eye Disorders: Frequent - conjunctivitis (including allergic); Infrequent – dry eye, blepharitis, eyelid edema, eye swelling, lenticular opacities, cataract, hyperemia (including conjunctival)

Gastrointestinal Disorders: Infrequent – gastritis, salivary hypersecretion, fecal incontinence, mouth ulceration; Rare - aphthous stomatitis, duodenal ulcer, hiatus hernia, hyperchlorhydria, lip ulceration, reflux esophagitis, stomatitis

General Disorders and Administrative Site Conditions: Infrequent – edema (general, pitting, due to cardiac disease), difficulty in walking, thirst; Rare - hyperthermia

Hepatobiliary Disorders: Infrequent – cholelithiasis

Investigations: Frequent: weight decreased; Infrequent – hemoglobin decreased, neutrophil count increased, hematocrit decreased

Metabolism and Nutrition Disorders: Infrequent – increased appetite, dehydration, hypokalemia, fluid retention

Musculoskeletal and Connective Tissue Disorders: Frequent – myalgia, muscle spasms; Rare – torticollis

Nervous System Disorders: Infrequent – paresthesia, psychomotor hyperactivity, restlessness, amnesia, nystagmus; Rare – restless legs syndrome

Psychiatric Disorders: Frequent – restlessness, aggression, delusion; Infrequent – hostility, libido decreased, paranoia, anorgasmia, confusional state, mania, catatonia, mood swings, panic attack, obsessive-compulsive disorder, bulimia nervosa, delirium, polydipsia psychogenic, impulse-control disorder, major depression

Renal and Urinary Disorders: Frequent – urinary incontinence; Infrequent – dysuria, pollakiuria, enuresis, nephrolithiasis; Rare – urinary retention, renal failure acute

Reproductive System and Breast Disorders: Frequent – erectile dysfunction; Infrequent – testicular pain, amenorrhea, breast pain; Rare – menstruation irregular, gynecomastia, menorrhagia, metrorrhagia, postmenopausal hemorrhage, prostatitis.

Respiratory, Thoracic and Mediastinal Disorders: Infrequent – epistaxis, asthma, rhinorrhea, sinus congestion, nasal dryness; Rare – dry throat, sleep apnea syndrome, dyspnea exertional

6.2 Postmarketing Experience

The following adverse reactions have been identified during post-approval use of FANAPT: retrograde ejaculation and hypersensitivity reactions (including anaphylaxis; angioedema; throat tightness; oropharyngeal swelling; swelling of the face, lips, mouth, and tongue; urticaria; rash; and pruritus). Because these reactions were reported voluntarily from a population of uncertain size, it is not possible to reliably estimate their frequency or establish a causal relationship to drug exposure.

7 DRUG INTERACTIONS

Given the primary CNS effects of FANAPT, caution should be used when it is taken in combination with other centrally acting drugs and alcohol. Due to its - alpha1-adrenergic receptor antagonism, FANAPT has the potential to enhance the effect of certain antihypertensive agents.

7.1 Potential for Other Drugs to Affect FANAPT

Iloperidone is not a substrate for CYP1A1, CYP1A2, CYP2A6, CYP2B6, CYP2C8, CYP2C9, CYP2C19, or CYP2E1 enzymes. This suggests that an interaction of iloperidone with inhibitors or inducers of these enzymes, or other factors, like smoking, is unlikely.

Both CYP3A4 and CYP2D6 are responsible for iloperidone metabolism. Inhibitors of CYP3A4 (e.g., ketoconazole) or CYP2D6 (e.g., fluoxetine, paroxetine) can inhibit iloperidone elimination and cause increased blood levels.

Ketoconazole: Co-administration of ketoconazole (200 mg twice daily for 4 days), a potent inhibitor of CYP3A4, with a 3 mg single dose of iloperidone to 19 healthy volunteers, ages 18-45 years, increased the area under the curve (AUC) of iloperidone and its metabolites P88 and P95 by 57%, 55% and 35%, respectively. Iloperidone doses should be reduced by about one-half when administered with ketoconazole or other strong inhibitors of CYP3A4 (e.g., itraconazole). Weaker inhibitors (e.g., erythromycin, grapefruit juice) have not been studied. When the CYP3A4 inhibitor is withdrawn from the combination therapy, the iloperidone dose should be returned to the previous level.

Fluoxetine: Coadministration of fluoxetine (20 mg twice daily for 21 days), a potent inhibitor of CYP2D6, with a single 3 mg dose of iloperidone to 23 healthy volunteers, ages 29-44 years, who were classified as CYP2D6 extensive metabolizers, increased the AUC of iloperidone and its metabolite P88, by about 2- to 3-fold, and decreased the AUC of its metabolite P95 by one-half. Iloperidone doses should be reduced by one-half when administered with fluoxetine. When fluoxetine is withdrawn from the combination therapy, the iloperidone dose should be returned to the previous level. Other strong inhibitors of CYP2D6 would be expected to have similar effects and would need appropriate dose reductions. When the CYP2D6 inhibitor is withdrawn from the combination therapy, iloperidone dose could then be increased to the previous level.

Paroxetine: Coadministration of paroxetine (20 mg/day for 5-8 days), a potent inhibitor of CYP2D6, with multiple doses of iloperidone (8 or 12 mg twice daily) to patients with schizophrenia ages 18-65 years resulted in increased mean steady-state peak concentrations of iloperidone and its metabolite P88, by about 1.6 fold, and decreased mean steady-state peak concentrations of its metabolite P95 by one-half. Iloperidone doses should be reduced by one-half when administered with paroxetine. When paroxetine is withdrawn from the combination therapy, the iloperidone dose should be returned to the previous level. Other strong inhibitors of CYP2D6 would be expected to have similar effects and would need appropriate dose reductions. When the CYP2D6 inhibitor is withdrawn from the combination therapy, iloperidone dose could then be increased to previous levels.

Paroxetine and Ketoconazole: Coadministration of paroxetine (20 mg once daily for 10 days), a CYP2D6 inhibitor, and ketoconazole (200 mg twice daily) with multiple doses of iloperidone (8 or 12 mg twice daily) to patients with schizophrenia ages 18-65 years resulted in a 1.4 fold increase in steady-state concentrations of iloperidone and its metabolite P88 and a 1.4 fold decrease in the P95 in the presence of paroxetine. So giving iloperidone with inhibitors of both of its metabolic pathways did not add to the effect of either inhibitor given alone. Iloperidone doses should therefore be reduced by about one-half if administered concomitantly with both a CYP2D6 and CYP3A4 inhibitor.

7.2 Potential for FANAPT to Affect Other Drugs

In vitro studies in human liver microsomes showed that iloperidone does not substantially inhibit the metabolism of drugs metabolized by the following cytochrome P450 isozymes: CYP1A1, CYP1A2, CYP2A6, CYP2B6, CYP2C8, CYP2C9, or CYP2E1. Furthermore, in vitro studies in human liver microsomes showed that iloperidone does not have enzyme inducing properties, specifically for the following cytochrome P450 isozymes: CYP1A2, CYP2C8, CYP2C9, CYP2C19, CYP3A4 and CYP3A5.

Dextromethorphan: A study in healthy volunteers showed that changes in the pharmacokinetics of dextromethorphan (80 mg dose) when a 3 mg dose of iloperidone was co-administered resulted in a 17% increase in total exposure and a 26% increase in the maximum plasma concentrations Cmax of dextromethorphan. Thus, an interaction between iloperidone and other CYP2D6 substrates is unlikely.

Fluoxetine: A single 3 mg dose of iloperidone had no effect on the pharmacokinetics of fluoxetine (20 mg twice daily).

Midazolam (a sensitive CYP 3A4 substrate): A study in patients with schizophrenia showed a less than 50% increase in midazolam total exposure at iloperidone steady state (14 days of oral dosing at up to 10 mg iloperidone twice daily) and no effect on midazolam Cmax. Thus, an interaction between iloperidone and other CYP3A4 substrates is unlikely.

7.3 Drugs that Prolong the QT Interval

FANAPT should not be used with any other drugs that prolong the QT interval [see Warnings and Precautions (5.2)].

8 USE IN SPECIFIC POPULATIONS

8.1 Pregnancy

Pregnancy Category C

FANAPT caused developmental toxicity, but was not teratogenic, in rats and rabbits.

In an embryo-fetal development study, pregnant rats were given 4, 16, or 64 mg/kg/day (1.6, 6.5, and 26 times the maximum recommended human dose (MRHD) of 24 mg/day on a mg/m^2 basis) of iloperidone orally during the period of organogenesis. The highest dose caused increased early intrauterine deaths, decreased fetal weight and length, decreased fetal skeletal ossification, and an increased incidence of minor fetal skeletal anomalies and variations; this dose also caused decreased maternal food consumption and weight gain.

In an embryo-fetal development study, pregnant rabbits were given 4, 10, or 25 mg/kg/day (3, 8, and 20 times the MRHD on a mg/m^2 basis) of iloperidone during the period of organogenesis. The highest dose caused increased early intrauterine deaths and decreased fetal viability at term; this dose also caused maternal toxicity.

In additional studies in which rats were given iloperidone at doses similar to the above beginning from either pre-conception or from day 17 of gestation and continuing through weaning, adverse reproductive effects included prolonged pregnancy and parturition, increased stillbirth rates, increased incidence of fetal visceral variations, decreased fetal and pup weights, and decreased post-partum pup survival. There were no drug effects on the neurobehavioral or reproductive development of the surviving pups. No-effect doses ranged from 4 to 12 mg/kg except for the increase in stillbirth rates which occurred at the lowest dose tested of 4 mg/kg, which is 1.6 times the MRHD on a mg/m^2 basis. Maternal toxicity was seen at the higher doses in these studies.

The iloperidone metabolite P95, which is a major circulating metabolite of iloperidone in humans but is not present in significant amounts in rats, was given to pregnant rats during the period of organogenesis at oral doses of 20, 80, or 200 mg/kg/day. No teratogenic effects were seen. Delayed skeletal ossification occurred at all doses. No significant maternal toxicity was produced. Plasma levels of P95 (AUC) at the highest dose tested were 2 times those in humans receiving the MRHD of iloperidone.

There are no adequate and well-controlled studies in pregnant women.

Non-teratogenic Effects

Neonates exposed to antipsychotic drugs, during the third trimester of pregnancy are at risk for extrapyramidal and/or withdrawal symptoms following delivery. There have been reports of agitation, hypertonia, hypotonia, tremor, somnolence, respiratory distress and feeding disorder in these neonates. These complications have varied in severity; while in some cases symptoms have been self-limited, in other cases neonates have required intensive care unit support and prolonged hospitalization.

FANAPT should be used during pregnancy only if the potential benefit justifies the potential risk to the fetus.

8.2 Labor and Delivery

The effect of FANAPT on labor and delivery in humans is unknown.

8.3 Nursing Mothers

FANAPT was excreted in milk of rats during lactation. It is not known whether FANAPT or its metabolites are excreted in human milk. It is recommended that women receiving FANAPT should not breast-feed.

8.4 Pediatric Use

Safety and effectiveness in pediatric and adolescent patients have not been established.

8.5 Geriatric Use

Clinical Studies of FANAPT in the treatment of schizophrenia did not include sufficient numbers of patients aged 65 years and over to determine whether or not they respond differently than younger adult patients. Of the 3210 patients treated with FANAPT in premarketing trials, 25 (0.5%) were ≥65 years old and there were no patients ≥75 years old.

Studies of elderly patients with psychosis associated with Alzheimer’s disease have suggested that there may be a different tolerability profile (i.e., increased risk in mortality and cerebrovascular events including stroke) in this population compared to younger patients with schizophrenia [see Boxed Warning and Warnings and Precautions (5.1)]. The safety and efficacy of FANAPT in the treatment of patients with psychosis associated with Alzheimer’s disease has not been established. If the prescriber elects to treat such patients with FANAPT, vigilance should be exercised.

8.6 Renal Impairment

Because FANAPT is highly metabolized, with less than 1% of the drug excreted unchanged, renal impairment alone is unlikely to have a significant impact on the pharmacokinetics of FANAPT. Renal impairment (creatinine clearance <30 mL/min) had minimal effect on Cmax of iloperidone (given in a single dose of 3 mg) and its metabolites P88 and P95 in any of the 3analytes measured. AUC0–∞ was increased by 24%, decreased by 6%, and increased by 52% for iloperidone, P88 and P95, respectively, in subjects with renal impairment.

8.7 Hepatic Impairment

No dose adjustment to FANAPT is needed in patients with mild hepatic impairment. Exercise caution when administering it to patients with moderate hepatic impairment. FANAPT is not recommended for patients with severe hepatic impairment [see Dosage in Special Populations (2.2)].

In adult subjects with mild hepatic impairment no relevant difference in pharmacokinetics of iloperidone, P88 or P95 (total or unbound) was observed compared to healthy adult controls. In subjects with moderate hepatic impairment a higher (2-fold) and more variable free exposure to the active metabolites P88 was observed compared to healthy controls, whereas exposure to iloperidone and P95 was generally similar (less than 50% change compared to control). Since a study in severe liver impaired subjects has not been conducted, FANAPT is not recommended for patients with severe hepatic impairment.

8.8 Smoking Status

Based on in vitro studies utilizing human liver enzymes, FANAPT is not a substrate for CYP1A2; smoking should therefore not have an effect on the pharmacokinetics of FANAPT.

9 DRUG ABUSE AND DEPENDENCE

9.1 Controlled Substance

FANAPT is not a controlled substance.

9.2 Abuse

FANAPT has not been systematically studied in animals or humans for its potential for abuse, tolerance, or physical dependence. While the clinical trials did not reveal any tendency for drug-seeking behavior, these observations were not systematic and it is not possible to predict on the basis of this experience the extent to which a CNS active drug, FANAPT, will be misused, diverted, and/or abused once marketed. Consequently, patients should be evaluated carefully for a history of drug abuse, and such patients should be observed closely for signs of FANAPT misuse or abuse (e.g. development of tolerance, increases in dose, drug-seeking behavior).

10 OVERDOSAGE

10.1 Human Experience

In pre-marketing trials involving over 3210 patients, accidental or intentional overdose of FANAPT was documented in 8 patients ranging from 48 mg to 576 mg taken at once and 292 mg taken over a 3-day period. No fatalities were reported from these cases. The largest confirmed single ingestion of FANAPT was 576 mg; no adverse physical effects were noted for this patient. The next largest confirmed ingestion of FANAPT was 438 mg over a 4-day period; extrapyramidal symptoms and a QTc interval of 507 msec were reported for this patient with no cardiac sequelae. This patient resumed FANAPT treatment for an additional 11 months. In general, reported signs and symptoms were those resulting from an exaggeration of the known pharmacological effects (e.g., drowsiness and sedation, tachycardia and hypotension) of FANAPT.

10.2 Management of Overdose

There is no specific antidote for FANAPT. Therefore appropriate supportive measures should be instituted. In case of acute overdose, the physician should establish and maintain an airway and ensure adequate oxygenation and ventilation. Gastric lavage (after intubation, if patient is unconscious) and administration of activated charcoal together with a laxative should be considered. The possibility of obtundation, seizures or dystonic reaction of the head and neck following overdose may create a risk of aspiration with induced emesis. Cardiovascular monitoring should commence immediately and should include continuous ECG monitoring to detect possible arrhythmias. If antiarrhythmic therapy is administered, disopyramide, procainamide and quinidine should not be used, as they have the potential for QT-prolonging effects that might be additive to those of FANAPT. Similarly, it is reasonable to expect that the alpha-blocking properties of bretylium might be additive to those of FANAPT, resulting in problematic hypotension. Hypotension and circulatory collapse should be treated with appropriate measures such as intravenous fluids or sympathomimetic agents (epinephrine and dopamine should not be used, since beta stimulation may worsen hypotension in the setting of FANAPT-induced alpha blockade). In cases of severe extrapyramidal symptoms, anticholinergic medication should be administered. Close medical supervision should continue until the patient recovers.

11 DESCRIPTION

FANAPT is a psychotropic agent belonging to the chemical class of piperidinyl-benzisoxazole derivatives. Its chemical name is 4’-[3-[4-(6-Fluoro-1,2-benzisoxazol-3-yl)piperidino]propoxy]-3’-methoxyacetophenone. Its molecular formula is C24H27FN2O4 and its molecular weight is 426.48. The structural formula is:

Iloperidone is a white to off-white finely crystalline powder. It is practically insoluble in water, very slightly soluble in 0.1 N HCl and freely soluble in chloroform, ethanol, methanol, and acetonitrile.

FANAPT tablets are intended for oral administration only. Each round, uncoated tablet contains 1 mg, 2 mg, 4 mg, 6 mg, 8 mg, 10 mg, or 12 mg of iloperidone. Inactive ingredients are: lactose monohydrate, microcrystalline cellulose, hydroxypropylmethylcellulose, crospovidone, magnesium stearate, colloidal silicon dioxide, and purified water (removed during processing). The tablets are white, round, flat, beveled-edged and identified with a logo “” debossed on one side and tablet strength “1”, “2”, “4”, “6”, “8”, “10”, or “12” debossed on the other side.

12 CLINICAL PHARMACOLOGY

12.1 Mechanism of Action

The mechanism of action of FANAPT, as with other drugs having efficacy in schizophrenia, is unknown. However it is proposed that the efficacy of FANAPT is mediated through a combination of dopamine type 2 (D2) and serotonin type 2 (5-HT2) antagonisms.

12.2 Pharmacodynamics

FANAPT exhibits high (nM) affinity binding to serotonin 5-HT2Adopamine D2 and D3 receptors, and norepinephrine NEα1 receptors (Ki values of 5.6, 6.3, 7.1, and 0.36 nM, respectively). FANAPT has moderate affinity for dopamine D4, and serotonin 5-HT6 and 5-HT7receptors (Ki values of 25, 43, and 22, nM respectively), and low affinity for the serotonin 5-HT1A, dopamine D1, and histamine H1 receptors (Ki values of 168, 216 and 437 nM, respectively). FANAPT has no appreciable affinity (Ki >1000 nM) for cholinergic muscarinic receptors. FANAPT functions as an antagonist at the dopamine D2, D3, serotonin 5-HT1A and norepinephrine α1/α2C receptors. The affinity of the FANAPT metabolite P88 is generally equal or less than that of the parent compound. In contrast, the metabolite P95 only shows affinity for 5-HT2A (Ki value of 3.91) and the NEα1A, NEα1B, NEα1D, and NEα2C receptors (Ki values of 4.7, 2.7, 8.8 and 4.7 nM respectively).

12.3 Pharmacokinetics

The observed mean elimination half-lives for iloperidone, P88 and P95 in CYP2D6 extensive metabolizers (EM) are 18, 26, and 23 hours, respectively, and in poor metabolizers (PM) are 33, 37 and 31 hours, respectively. Steady-state concentrations are attained within 3-4 days of dosing. Iloperidone accumulation is predictable from single-dose pharmacokinetics. The pharmacokinetics of iloperidone is more than dose proportional. Elimination of iloperidone is mainly through hepatic metabolism involving 2 P450 isozymes, CYP2D6 and CYP3A4.

Absorption: Iloperidone is well absorbed after administration of the tablet with peak plasma concentrations occurring within 2 to 4 hours; while the relative bioavailability of the tablet formulation compared to oral solution is 96%. Administration of iloperidone with a standard high-fat meal did not significantly affect the Cmax or AUC of iloperidone, P88, or P95, but delayed Tmax by 1 hour for iloperidone, 2 hours for P88 and 6 hours for P95. FANAPT can be administered without regard to meals.

Distribution: Iloperidone has an apparent clearance (clearance/bioavailability) of 47 to 102 L/h, with an apparent volume of distribution of 1340-2800 L. At therapeutic concentrations, the unbound fraction of iloperidone in plasma is ~3% and of each metabolite (P88 and P95) it is ~8%.

Metabolism and Elimination: Iloperidone is metabolized primarily by 3 biotransformation pathways: carbonyl reduction, hydroxylation (mediated by CYP2D6) and O-demethylation (mediated by CYP3A4). There are 2 predominant iloperidone metabolites, P95 and P88. The iloperidone metabolite P95 represents 47.9% of the AUC of iloperidone and its metabolites in plasma at steady-state for extensive metabolizers (EM) and 25% for poor metabolizers (PM). The active metabolite P88 accounts for 19.5% and 34.0% of total plasma exposure in EM and PM, respectively.

Approximately 7% - 10% of Caucasians and 3% - 8% of black/African Americans lack the capacity to metabolize CYP2D6 substrates and are classified as poor metabolizers (PM), whereas the rest are intermediate, extensive or ultrarapid metabolizers. Coadministration of FANAPT with known strong inhibitors of CYP2D6 like fluoxetine results in a 2.3-fold increase in iloperidone plasma exposure, and therefore one-half of the FANAPT dose should be administered.

Similarly, PMs of CYP2D6 have higher exposure to iloperidone compared with EMs and PMs should have their dose reduced by one-half. Laboratory tests are available to identify CYP2D6 PMs.

The bulk of the radioactive materials were recovered in the urine (mean 58.2% and 45.1% in EM and PM, respectively), with feces accounting for 19.9% (EM) to 22.1% (PM) of the dosed radioactivity.

Transporter Interaction: Iloperidone and P88 are not substrates of P-gp and iloperidone is a weak P-gp inhibitor.

13 NONCLINICAL TOXICOLOGY

13.1 Carcinogenesis, Mutagenesis, Impairment of Fertility

Carcinogenesis: Lifetime carcinogenicity studies were conducted in CD-1 mice and Sprague Dawley rats. Iloperidone was administered orally at doses of 2.5, 5.0 and 10 mg/kg/day to CD-1 mice and 4, 8, and 16 mg/kg/day to Sprague Dawley rats (0.5, 1.0 and 2.0 times and 1.6, 3.2 and 6.5 times, respectively, the MRHD of 24 mg/day on a mg/m^2 basis). There was an increased incidence of malignant mammary gland tumors in female mice treated with the lowest dose (2.5 mg/kg/day) only. There were no treatment-related increases in neoplasia in rats.

The carcinogenic potential of the iloperidone metabolite P95, which is a major circulating metabolite of iloperidone in humans but is not present at significant amounts in mice or rats, was assessed in a lifetime carcinogenicity study in Wistar rats at oral doses of 25, 75 and 200 mg/kg/day in males and 50, 150, and 250 (reduced from 400) mg/kg/day in females.

Drug-related neoplastic changes occurred in males, in the pituitary gland (pars distalis adenoma) at all doses and in the pancreas (islet cell adenoma) at the high dose. Plasma levels of P95 (AUC) in males at the tested doses (25, 75, and 200 mg/kg/day) were approximately 0.4, 3, and 23 times, respectively, the human exposure to P95 at the MRHD of iloperidone.

An increase in mammary, pituitary and endocrine pancreas neoplasms has been found in rodents after chronic administration of other antipsychotic drugs and is considered to be mediated by prolonged dopamine D2 antagonism and hyperprolactinemia. Increases in serum prolactin were seen in mice and rats treated with iloperidone. The relevance of these tumor findings in rodents in terms of human risk is unknown.

Mutagenesis: Iloperidone was negative in the Ames test and in the in vivo mouse bone marrow and rat liver micronucleus tests. Iloperidone induced chromosomal aberrations in Chinese Hamster Ovary (CHO) cells in vitro at concentrations which also caused some cytotoxicity.

The iloperidone metabolite P95 was negative in the Ames test, the V79 chromosome aberration test, and an in vivo mouse bone marrow micronucleus test.

Impairment of Fertility: Iloperidone decreased fertility at 12 and 36 mg/kg in a study in which both male and female rats were treated. The no-effect dose was 4 mg/kg, which is 1.6 times the MRHD of 24 mg/day on a mg/m^2 basis.

14 CLINICAL STUDIES

The efficacy of FANAPT in the treatment of schizophrenia was supported by 2 placebo- and active-controlled short-term (4- and 6-week) trials. Both trials enrolled patients who met the DSM-III/IV criteria for schizophrenia.

Two instruments were used for assessing psychiatric signs and symptoms in these studies. The Positive and Negative Syndrome Scale (PANSS) and Brief Psychiatric Rating Scale (BPRS) are both multi-item inventories of general psychopathology usually used to evaluate the effects of drug treatment in schizophrenia.

A 6-week, placebo-controlled trial (n=706) involved 2 flexible dose ranges of FANAPT (12-16 mg/day or 20-24 mg/day) compared to placebo and an active control (risperidone). For the 12-16 mg/day group, the titration schedule of FANAPT was 1 mg twice daily on Days 1 and 2, 2 mg twice daily on Days 3 and 4, 4 mg twice daily on Days 5 and 6, and 6 mg twice daily on Day 7. For the 20-24 mg/day group, the titration schedule of FANAPT was 1 mg twice daily on Day 1, 2 mg twice daily on Day 2, 4 mg twice daily on Day 3, 6 mg twice daily on Days 4 and 5, 8 mg twice daily on Day 6, and 10 mg twice daily on Day 7. The primary endpoint was change from baseline on the BPRS total score at the end of treatment (Day 42). Both the 12-16 mg/day and the 20-24 mg/day dose ranges of FANAPT were superior to placebo on the BPRS total score. The active control antipsychotic drug appeared to be superior to FANAPT in this trial within the first 2 weeks, a finding that may in part be explained by the more rapid titration that was possible for that drug. In patients in this study who remained on treatment for at least 2 weeks, iloperidone appeared to have had comparable efficacy to the active control.

A 4-week, placebo-controlled trial (n=604) involved one fixed dose of FANAPT (24 mg/day) compared to placebo and an active control (ziprasidone). The titration schedule for this study was similar to that for the 6-week study. This study involved titration of FANAPT starting at 1 mg twice daily on Day 1 and increasing to 2, 4, 6, 8, 10 and 12 mg twice daily on Days 2, 3, 4, 5, 6, and 7. The primary endpoint was change from baseline on the PANSS total score at the end of treatment (Day 28). The 24 mg/day FANAPT dose was superior to placebo in the PANSS total score. FANAPT appeared to have similar efficacy to the active control drug which also needed a slow titration to the target dose.

16 HOW SUPPLIED/STORAGE AND HANDLING

FANAPT tablets are white, round and identified with a logo “” debossed on one side and tablet strength “4” debossed on the other side. Tablets are supplied in the following strengths and package configurations:

NDC 69189-0665-1 single dose pack with 1 tablet as repackaged by Avera McKennan Hospital

Package Configuration | Tablet Strength (mg) | NDC Code
Bottles of 60 | 4 mg | 43068-104-02

Storage

Store FANAPT tablets at controlled room temperature, 25°C (77°F); excursions permitted to 15°to 30 °C (59° to 86°F) [See USP Controlled Room Temperature]. Protect FANAPT tablets from exposure to light and moisture.

17 PATIENT COUNSELING INFORMATION

Physicians are advised to discuss the following issues with patients for whom they prescribe FANAPT:

17.1 QT Interval Prolongation

Patients should be advised to consult their physician immediately if they feel faint, lose consciousness or have heart palpitations. Patients should be counseled not to take FANAPT with other drugs that cause QT interval prolongation [see Warnings and Precautions (5.2)]. Patients should be told to inform physicians that they are taking FANAPT before any new drug is taken.

17.2 Neuroleptic Malignant Syndrome

Patients and caregivers should be counseled that a potentially fatal symptom complex sometimes referred to as NMS has been reported in association with administration of antipsychotic drugs, including FANAPT. Signs and symptoms of NMS include hyperpyrexia, muscle rigidity, altered mental status, and evidence of autonomic instability (irregular pulse or blood pressure, tachycardia, diaphoresis, and cardiac dysrhythmia) [see Warnings and Precautions (5.3)].

17.3 Metabolic Changes

Patients should be aware of the symptoms of hyperglycemia (high blood sugar) and diabetes mellitus. Patients who are diagnosed with diabetes, those with risk factors for diabetes, or those who develop these symptoms during treatment should have their blood glucose monitored at the beginning of and periodically during treatment. Patients should be counseled that weight gain has occurred during treatment with FANAPT. Clinical monitoring of weight is recommended. [see Warnings and Precautions (5.5)].

17.4 Orthostatic Hypotension

Patients should be advised of the risk of orthostatic hypotension, particularly at the time of initiating treatment, re-initiating treatment, or increasing the dose [see Warnings and Precautions (5.7)].

17.5 Interference with Cognitive and Motor Performance

Because FANAPT may have the potential to impair judgment, thinking, or motor skills, patients should be cautioned about operating hazardous machinery, including automobiles, until they are reasonably certain that FANAPT therapy does not affect them adversely [see Warnings and Precautions (5.14)].

17.6 Pregnancy

Patients should be advised to notify their physician if they become pregnant or intend to become pregnant during therapy with FANAPT [see Use in Specific Populations (8.1)].

17.7 Nursing

Patients should be advised not to breastfeed an infant if they are taking FANAPT [see Use in Specific Populations (8.3)].

17.8 Concomitant Medication

Patients should be advised to inform their physicians if they are taking, or plan to take, any prescription or over-the-counter drugs, since there is a potential for interactions [see Drug Interactions (7)].

17.9 Alcohol

Patients should be advised to avoid alcohol while taking FANAPT.

17.10 Heat Exposure and Dehydration

Patients should be advised regarding appropriate care in avoiding overheating and dehydration.

Distributed by:

Vanda Pharmaceuticals Inc.

Washington, D.C. 20037 USA

Vanda and Fanapt® are registered trademarks of Vanda Pharmaceuticals Inc. in the United States and other countries.

January 2016